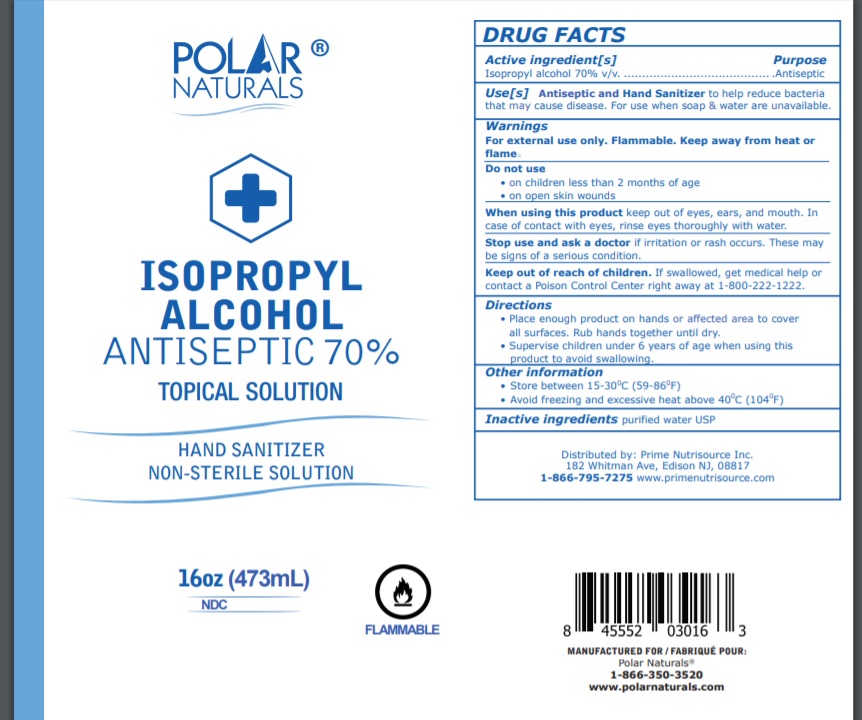 DRUG LABEL: BENEMAX ADVANCED Hand Sanitizer
NDC: 73700-004 | Form: LIQUID
Manufacturer: Nugale Pharmaceutical Inc
Category: otc | Type: HUMAN OTC DRUG LABEL
Date: 20210311

ACTIVE INGREDIENTS: ISOPROPYL ALCOHOL 70 mL/100 mL
INACTIVE INGREDIENTS: WATER

Drug Facts

Active ingredient

Isopropyl alcohol 70%, USP

Purpose

Antiseptic

Warnings

For external use only. Flammable. Keep away from heat or flame.

Do not use
• on children less than 2 months of age
• on open skin wounds

When using this product keep out of eyes, ears, and mouth. In
case of contact with eyes, rinse eyes thoroughly with water.

Stop use and ask a doctor if irritation or rash occurs. These may
be signs of a serious condition.

Directions

• Place enough product on hands or affected area to cover all surfaces. Rub hands together until dry.
• Supervise children under 6 years of age when using this product to avoid swallowing.

Uses

Antiseptic and Hand Sanitizer to help reduce bacteria that may cause disease. For use when soap & water are unavailable.

Keep out of reach of children

If swallowed, get medical help or contact a Poison Control Center right away at 1-800-222-1222.

Inactive ingredient

Water

Other information

Store between 15 °C and 30 °C. Avoid freezing and excessive heat above 400 °C (104 °F)